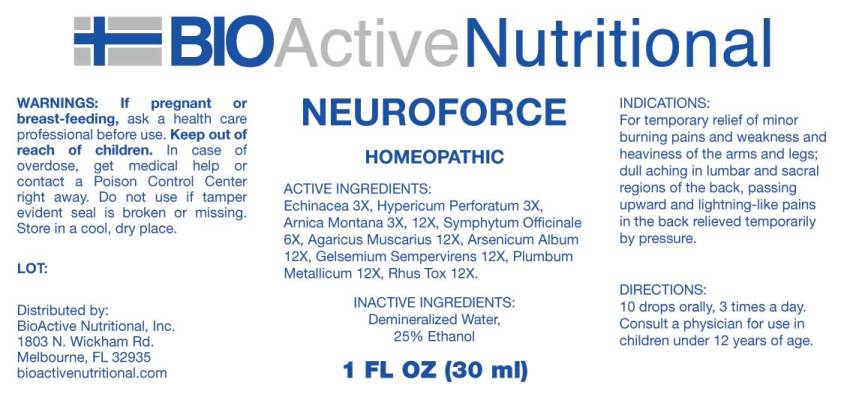 DRUG LABEL: Neuroforce
NDC: 43857-0457 | Form: LIQUID
Manufacturer: BioActive Nutritional, Inc.
Category: homeopathic | Type: HUMAN OTC DRUG LABEL
Date: 20170728

ACTIVE INGREDIENTS: ECHINACEA ANGUSTIFOLIA 3 [hp_X]/1 mL; HYPERICUM PERFORATUM 3 [hp_X]/1 mL; ARNICA MONTANA 3 [hp_X]/1 mL; COMFREY ROOT 6 [hp_X]/1 mL; AMANITA MUSCARIA FRUITING BODY 12 [hp_X]/1 mL; ARSENIC TRIOXIDE 12 [hp_X]/1 mL; GELSEMIUM SEMPERVIRENS ROOT 12 [hp_X]/1 mL; LEAD 12 [hp_X]/1 mL; TOXICODENDRON PUBESCENS LEAF 12 [hp_X]/1 mL
INACTIVE INGREDIENTS: WATER; ALCOHOL

Drug Facts:

ACTIVE INGREDIENTS:

Echinacea 3X, Hypericum Perforatum 3X, Arnica Montana 3X, Symphytum Officinale 6X, Agaricus Muscarius 12X, Arsenicum Album 12X, Gelsemium Sempervirens 12X, Plumbum Metallicum 12X, Rhus Tox 12X.

INDICATIONS:

For temporary relief of minor burning pains and weakness and heaviness of the arms and legs; dull aching in lumbar and sacral regions of the back, passing upward and lightning-like pains in the back relieved temporarily by pressure.

WARNINGS:

If pregnant or breast-feeding, ask a health care professional before use.

Keep out of reach of children. In case of overdose, get medical help or contact a Poison Control Center right away.

Do not use if tamper evident seal is broken or missing.

Store in a cool, dry place.

Keep out of reach of children. In case of overdose, get medical help or contact a Poison Control Center right away.

DIRECTIONS:

10 drops orally, 3 times a day. Consult a physician for use in children under 12 years of age.

INDICATIONS:

For temporary relief of minor burning pains and weakness and heaviness of the arms and legs; dull aching in lumbar and sacral regions of the back, passing upward and lightning-like pains in the back relieved temporarily by pressure.

INACTIVE INGREDIENTS:

Demineralized Water, 25% Ethanol

QUESTIONS:

Distributed by:

BioActive Nutritional, Inc.

1803 N. Wickham Rd.

Melbourne, FL 32935

bioactivenutritional.com

PACKAGE DISPLAY LABEL:

BIOActive Nutritional

NEUROFORCE

HOMEOPATHIC

1 FL OZ (30 ml)